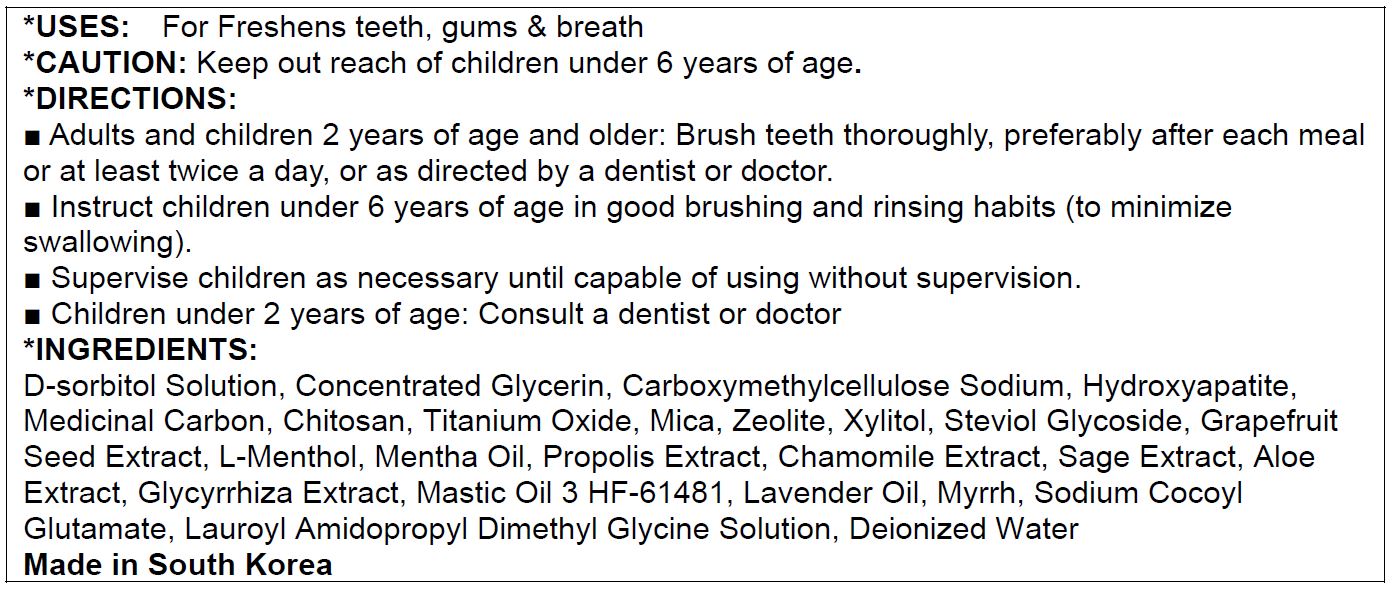 DRUG LABEL: Solmeet
NDC: 70706-1004 | Form: PASTE, DENTIFRICE
Manufacturer: SOLM Co., Ltd.
Category: otc | Type: HUMAN OTC DRUG LABEL
Date: 20191222

ACTIVE INGREDIENTS: CALCIUM CARBONATE 15.85 g/100 g
INACTIVE INGREDIENTS: GLYCERIN; ROSIN; WATER

Drug Facts

ACTIVE INGREDIENT

Calcium Carbonate

INACTIVE INGREDIENT

glycerine, rosin, water, etc.

PURPOSE

for dental care

keep out of reach of the children

INDICATIONS AND USAGE

use when is needed

WARNINGS

- do not swallow when using this product
- if more than used for rinsing is accidentally swallowed, get medical helps or contact a poison control center right away

DOSAGE AND ADMINISTRATION

apply proper amount on your toothbrush